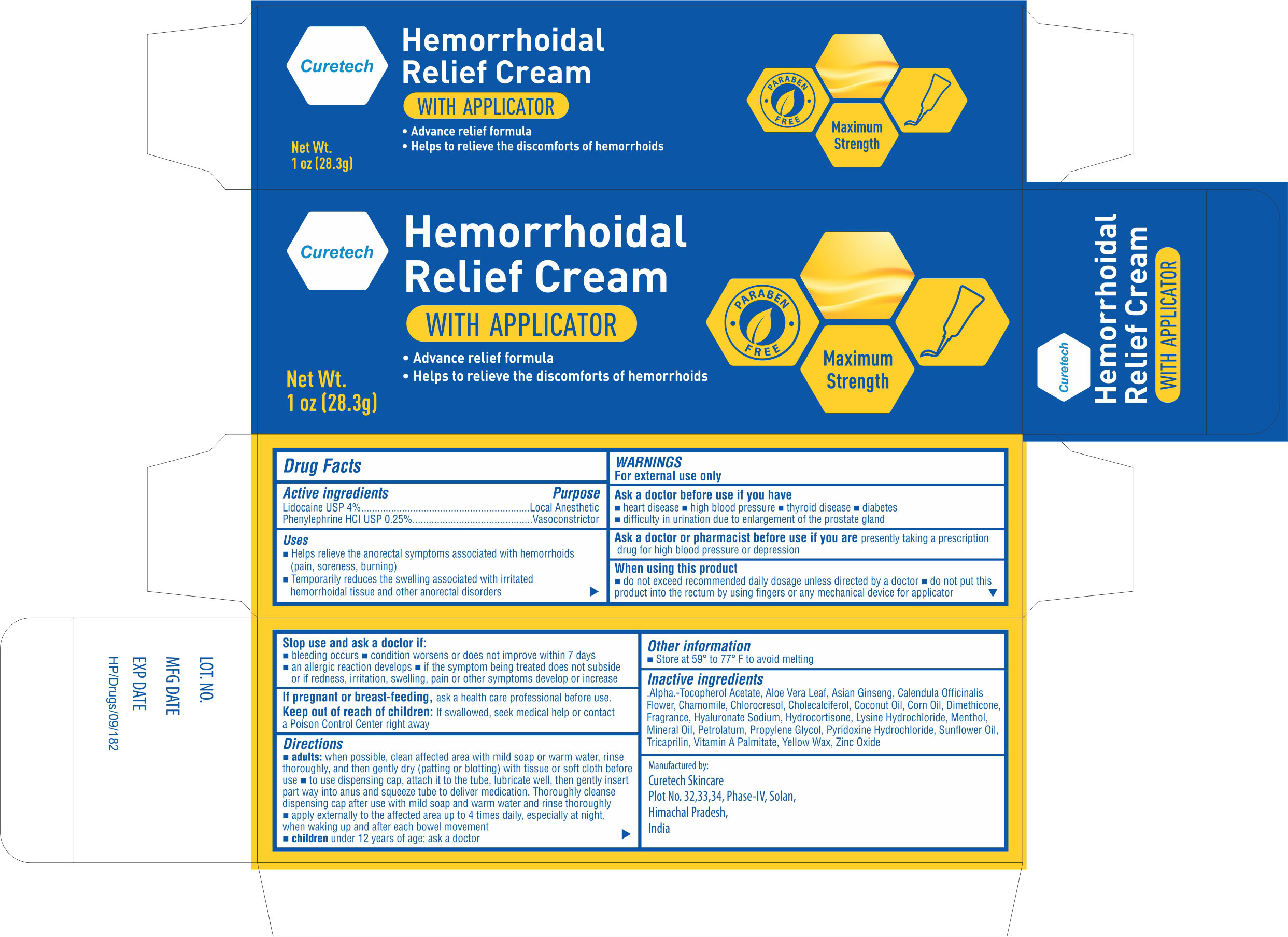 DRUG LABEL: Hemorrhoidal Relief Cream
NDC: 73622-3077 | Form: CREAM
Manufacturer: CURETECH SKINCARE
Category: otc | Type: HUMAN OTC DRUG LABEL
Date: 20210310

ACTIVE INGREDIENTS: PHENYLEPHRINE HYDROCHLORIDE 0.25 g/100 g; LIDOCAINE 4 g/100 g
INACTIVE INGREDIENTS: ALOE VERA LEAF; ASIAN GINSENG; CHAMOMILE; CHLOROCRESOL; CHOLECALCIFEROL; CORN OIL; DIMETHICONE; HYALURONATE SODIUM; LYSINE HYDROCHLORIDE; PROPYLENE GLYCOL; .ALPHA.-TOCOPHEROL ACETATE; YELLOW WAX; CALENDULA OFFICINALIS FLOWER; COCONUT OIL; HYDROCORTISONE; ZINC OXIDE; MINERAL OIL; PETROLATUM; TRICAPRILIN; MENTHOL; VITAMIN A PALMITATE; PYRIDOXINE HYDROCHLORIDE; SUNFLOWER OIL

Hemorrhoidal Relief Cream

Drug Facts

Active ingredients

Lidocaine USP 4%

Phenylephrine HCL USP 0.25%

Purpose

Lidocaine USP 4%--------------Local Anesthetic

Phenylephrine HCL USP 0.25%--Vasoconstrictor

Uses

- Helps relieve the anorectal symptoms associated with hemorrhoids (pain, soreness, burning)
- Temporarily reduces the swelling associated with irritated hemorrhoidal tissue and other anorectal disorders

WARNINGS

For external use only

Ask a doctor before use if you have

- heart Disease
- high blood pressure
- thyroid disease
- diabetes
- difficulty in urination due to enlargement of the prostate gland

Ask a doctor or pharmacist before use if you are

- presently taking a prescription drug for high blood pressure or depression

When using this product

- do not exceed recommended daily usage unless directed by a doctor
- do not put this product into the rectum by using fingers or any mechanical device or applicator

Stop use and ask a doctor if:

- bleeding occurs
- condition worsens or does not improve within 7 days
- an allergic reaction develops
- if symptoms being treated does not subside or if redness, irritation, swelling, pain or other symptoms develop or increase

If pregnant or breast-feeding

ask a healthcare professional before use

Keep out of reach of children:

If swallowed, seek medical help or contact a Poison Control Center right away

Directions

- adults: when possible, clean affected area with mild soap or warm water, rinse thoroughly, and then gently dry (patting or blotting) with tissue or soft cloth before use
- to use dispensing cap, attach it to the tube, lubricate well, then gentle insert part way into anus and squeeze tube to deliver medication. Thoroughly cleanse dispensing cap after use with mild soap and warm water and rinse thoroughly
- apply to affected area upto 4 times daily, especially at night, when waking up and after each bowel movement

Children under 12 years of age: ask a doctor

Other information

- store at 59 to 77 F to avoid melting

Inactive ingredients

.Alpha.-Tocopherol Acetate, Aloe Vera Leaf, Asian Ginseng, Calendula officinalis Flower, Chamomile, Chlorocresol, Cholecalciferol, Coconut Oil, Corn Oil, Dimethicone, Fragrance, Hyaluronate Sodium, Hydrocortisone, Lysine Hydrochloride, menthol, Mineral Oil, Petrolatum, Propylene Glycol, Pyridoxine Hydrochloride, Sunflower Oil, Tricaprilin, Vitamin A Palmitate, yellow Wax, Zinc Oxide